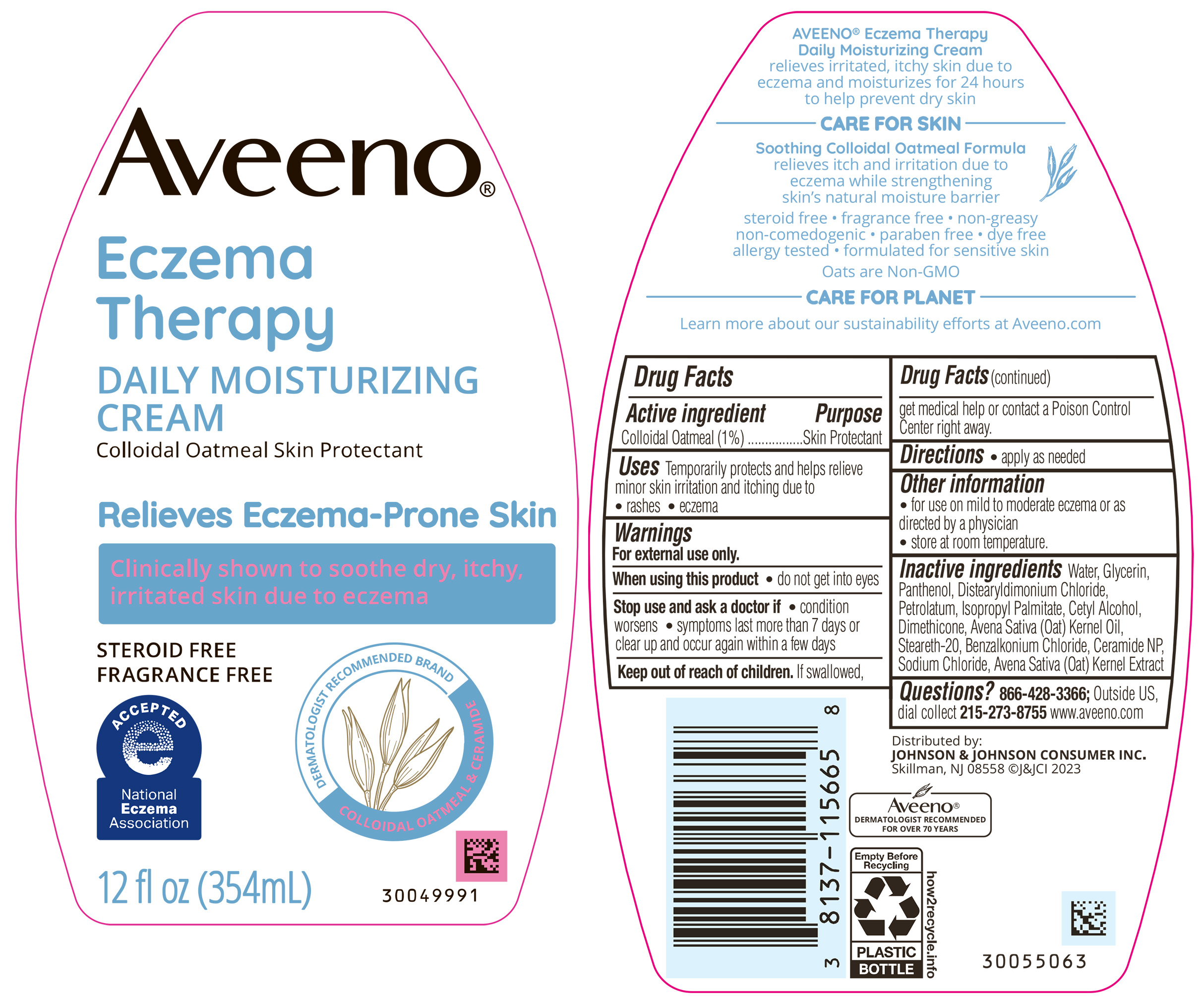 DRUG LABEL: Aveeno Eczema Therapy Daily Moisturizing
NDC: 69968-0774 | Form: CREAM
Manufacturer: Kenvue Brands LLC
Category: otc | Type: HUMAN OTC DRUG LABEL
Date: 20241105

ACTIVE INGREDIENTS: OATMEAL 10 mg/1 mL
INACTIVE INGREDIENTS: DISTEARYLDIMONIUM CHLORIDE; STEARETH-20; CERAMIDE NP; SODIUM CHLORIDE; DIMETHICONE; BENZALKONIUM CHLORIDE; OAT; WATER; GLYCERIN; PANTHENOL; PETROLATUM; ISOPROPYL PALMITATE; CETYL ALCOHOL; OAT KERNEL OIL

Aveeno Eczema Therapy Daily Moisturizing Cream

Drug Facts

Active Ingredient

Colloidal Oatmeal 1%

Purpose

Skin Protectant

Uses

Temporarily protects and helps relieve minor skin irritation and itching due to

• rashes • eczema

Warnings

For external use only.

When using this product

- do not get into eyes

Stop use and ask a doctor if

- condition worsens •symptoms last more than 7 days or clear up and occur again within a few days

Keep out of reach of children. If swallowed, get medical help or contact a Poison Control Center right away.

Directions

- apply as needed

Other Information

- for use on mild to moderate eczema or as directed by a physician
- store at room temperature.

Inactive Ingredients

Water, Glycerin, Panthenol, Distearyldimonium Chloride, Petrolatum, Isopropyl Palmitate, Cetyl Alcohol, Dimethicone, Avena Sativa (Oat) Kernel Oil, Steareth-20, Benzalkonium Chloride, Ceramide NP, Sodium Chloride, Avena Sativa (Oat) Kernel Extract

Questions?

866-428-3366; Outside US, dial collect 215-273-8755 www.aveeno.com

Distributed by:
JOHNSON & JOHNSON
CONSUMER INC.
Skillman, NJ 08558

PRINCIPAL DISPLAY PANEL - 354 mL Bottle

Aveeno®

Eczema

Therapy

DAILY MOISTURIZING

CREAM

Colloidal Oatmeal Skin Protectant

Relieves Eczema-Prone Skin

Clinically shown to soothe dry, itchy,

irritated skin due to eczema

STEROID FREE

FRAGRANCE FREE

ACCEPTED

e

National

Eczema

Association

DERMATOLOGIST RECOMMENDED BRAND

COLLOIDAL OATMEAL & CERAMIDE

12 fl oz (354mL)